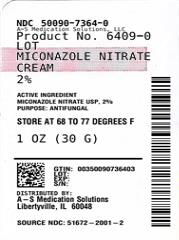 DRUG LABEL: Miconazole Nitrate
NDC: 50090-7364 | Form: CREAM
Manufacturer: A-S Medication Solutions
Category: otc | Type: HUMAN OTC DRUG LABEL
Date: 20251203

ACTIVE INGREDIENTS: MICONAZOLE NITRATE 20 mg/1 g
INACTIVE INGREDIENTS: APRICOT KERNEL OIL; BENZOIC ACID; BHT; GLYCOL STEARATE; PARAFFINUM LIQUIDUM; POLYETHYLENE GLYCOL 300; WATER; PEG-6 MONOSTEARATE; PEG-32 MONOSTEARATE

Miconazole Nitrate

Drug Facts

Active ingredient

Miconazole nitrate USP 2%

Purpose

Antifungal

Uses

- effective in the treatment of most athlete's foot (tinea pedis), jock itch (tinea cruris), and ringworm (tinea corporis)
- for effective relief of itching, scaling, burning and discomfort that can accompany these conditions.

Warnings

For external use only

DO NOT USE

Do not useon children less than 2 years of age unless directed by a doctor

When using this productavoid contact with eyes

Stop use and ask a doctor if

- irritation occurs
- condition persists
- there is no improvement of athlete's foot or ringworm within 4 weeks or jock itch within 2 weeks.

Keep out of reach of children.If swallowed, get medical help or contact a Poison Control Center right away (1-800-222-1222).

Directions

- clean the affected area and dry thoroughly
- apply a thin layer of the product over affected area twice daily (morning and night) or as directed by a doctor
- supervise children in the use of this product
- For athlete's foot: pay special attention to spaces between the toes; wear well-fitting, ventilated shoes, and change shoes and socks at least once daily
- For athlete's foot and ringworm: use daily for 4 weeks.
- For jock itch: use daily for 2 weeks
- not effective on the scalp or nails

Other information

- To open: unscrew cap, use pointed end on cap to puncture seal
- store at 20° - 25°C (68° - 77°F)
- see carton or tube crimp for lot number and expiration date

Inactive ingredients

apricot kernel oil, benzoic acid, BHT, glycol stearate, mineral oil, PEG-6, PEG-6-32 stearate, purified water

Questions?

Call 1-866-923-4914

Distributed by:
Taro Pharmaceuticals
U.S.A., Inc.
Hawthorne, NY 10532

HOW SUPPLIED

Product: 50090-7364

NDC: 50090-7364-0 30 g in a TUBE / 1 in a CARTON